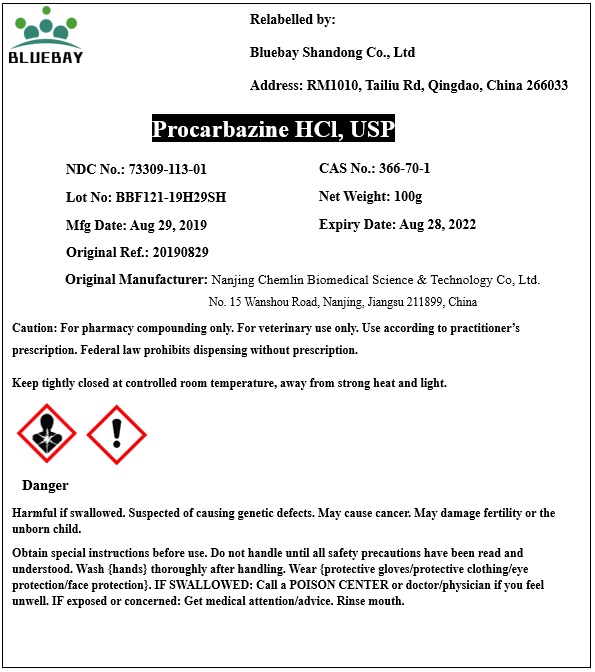 DRUG LABEL: Procarbazine Hydrochloride
NDC: 73309-113 | Form: POWDER
Manufacturer: BLUEBAY SHANDONG CO.,LTD
Category: other | Type: BULK INGREDIENT
Date: 20200409

ACTIVE INGREDIENTS: PROCARBAZINE HYDROCHLORIDE 1 g/1 g

Procarbazine Hydrochloride